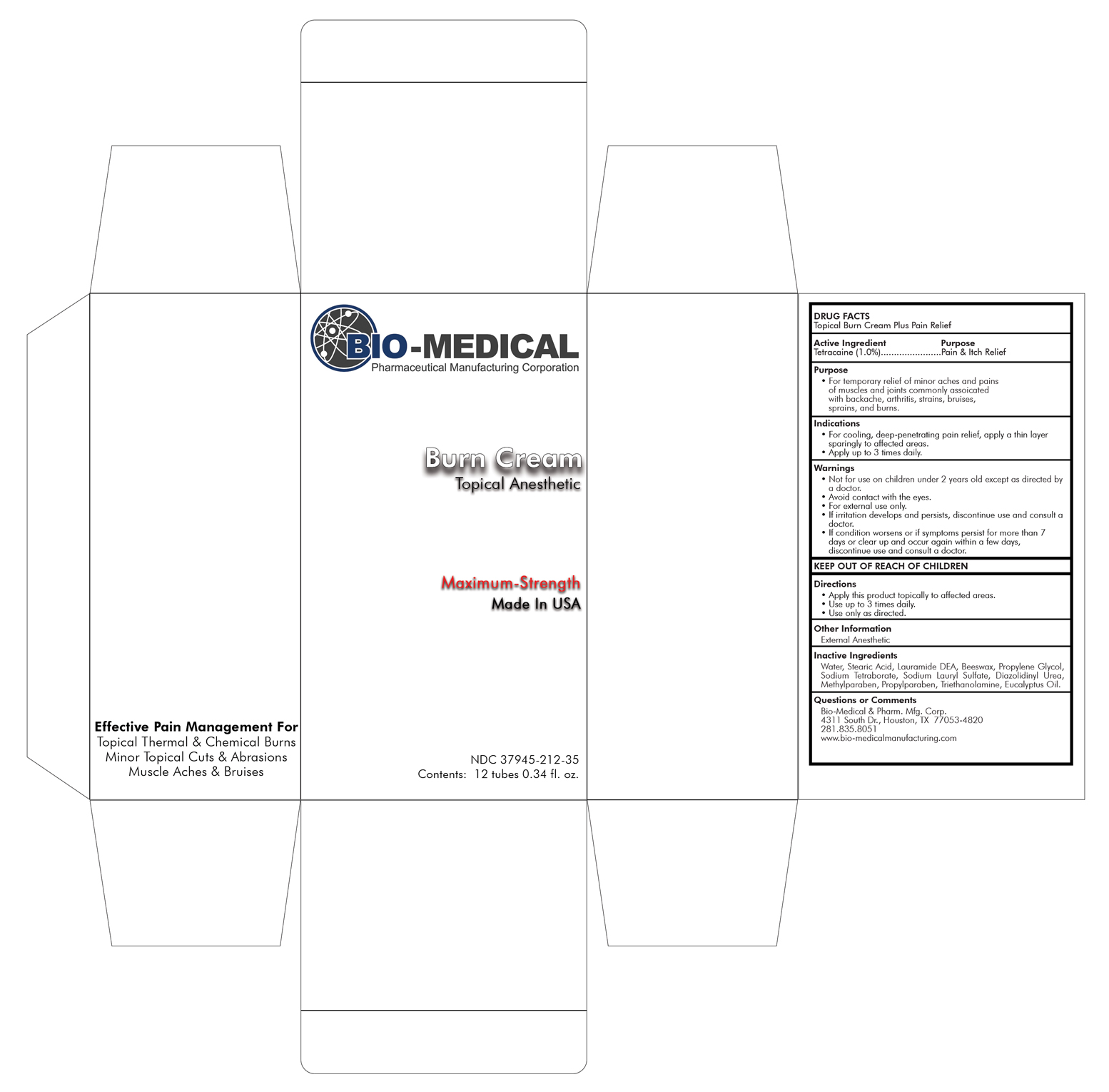 DRUG LABEL: Burn Cream
NDC: 37945-212 | Form: CREAM
Manufacturer: Bio-Medical & Pharmaceutical Manufacturing Corporation
Category: otc | Type: HUMAN OTC DRUG LABEL
Date: 20191218

ACTIVE INGREDIENTS: TETRACAINE 10 mg/1 mL
INACTIVE INGREDIENTS: YELLOW WAX; SODIUM BORATE ANHYDROUS; SODIUM LAURYL SULFATE; DIAZOLIDINYL UREA; METHYLPARABEN; PROPYLPARABEN; STEARIC ACID; LAURIC DIETHANOLAMIDE; PROPYLENE GLYCOL; TROLAMINE; EUCALYPTUS OIL; WATER

Drug Facts

Topical Burn Cream Plus Pain Relief

Active Ingredient

Active Ingredient Purpose

Tetracaine (1.0%).......................Pain & Itch Relief

Purpose

• For temporary relief of minor aches and pains of muscles and joints commonly assoicated with backache, arthritis, strains, bruises, sprains, and burns.

Indications

• For cooling, deep-penetrating pain relief, apply a thin layer sparingly to affected areas.
• Apply up to 3 times daily.

Warnings

• Not for use on children under 2 years old except as directed by
a doctor.
• Avoid contact with the eyes.
• For external use only.
• If irritation develops and persists, discontinue use and consult a
doctor.
• If condition worsens or if symptoms persist for more than 7 days or clear up and occur again within a few days, discontinue use and consult a doctor.

Directions

• Apply this product topically to affected areas.
• Use up to 3 times daily.
• Use only as directed.

Other Information

External Anesthetic

Inactive Ingredients

Water, Stearic Acid, Lauramide DEA, Beeswax, Propylene Glycol, Sodium Tetraborate, Sodium Lauryl Sulfate, Diazolidinyl Urea, Methylparaben, Propylparaben, Triethanolamine, Eucalyptus Oil.

Questions or Comments

Bio-Medical & Pharm. Mfg. Corp.
4311 South Dr., Houston, TX 77053-4820
281.835.8051 www.bio-medicalmanufacturing.com